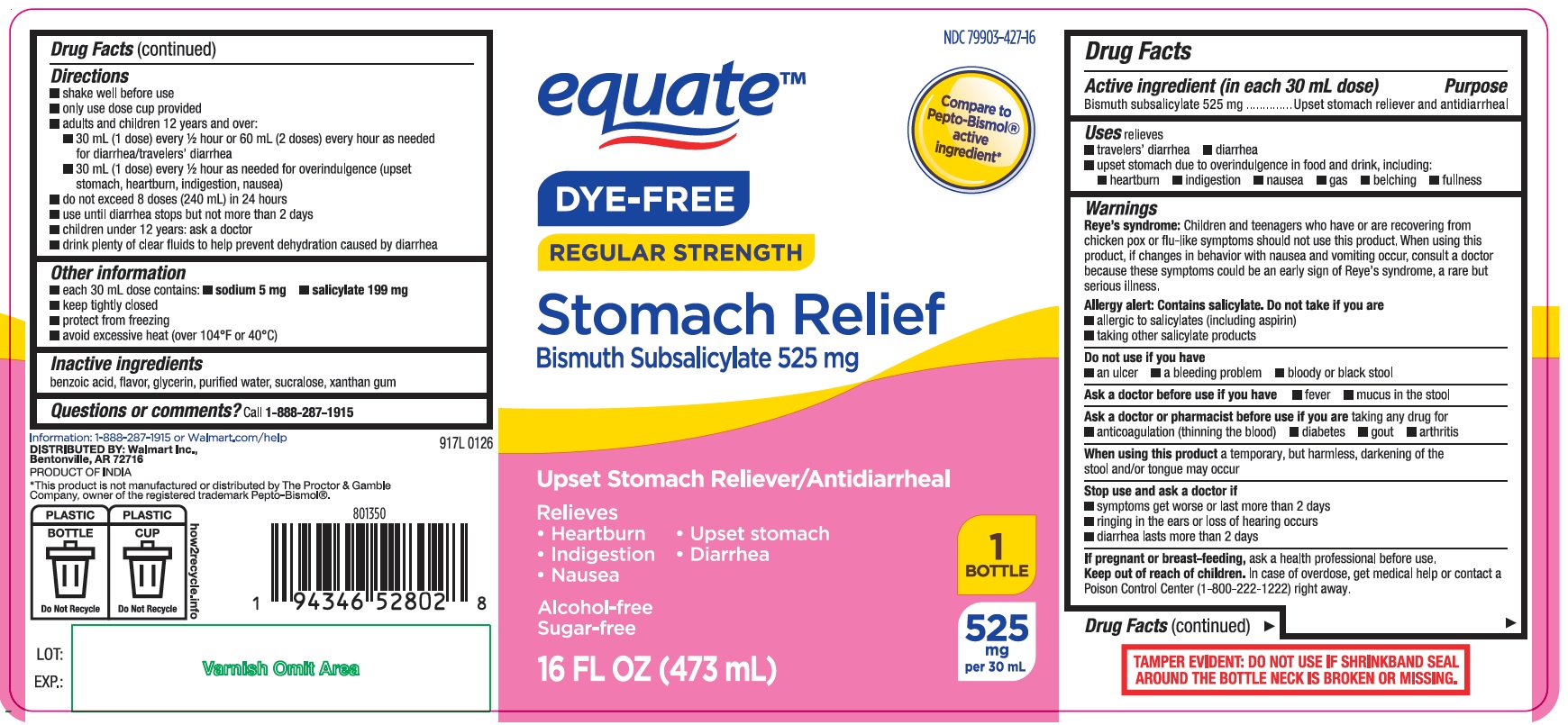 DRUG LABEL: Dye Free Regular Strength Stomach Relief
NDC: 79903-427 | Form: SUSPENSION
Manufacturer: Walmart Inc.
Category: otc | Type: HUMAN OTC DRUG LABEL
Date: 20260206

ACTIVE INGREDIENTS: BISMUTH SUBSALICYLATE 525 mg/30 mL
INACTIVE INGREDIENTS: SUCRALOSE; GLYCERIN; WATER; XANTHAN GUM; BENZOIC ACID

Bismuth subsalicylate 525mg/30mL Suspension Regular Strength - DYE FREE

Drug Facts

-

Active ingredient (in each 30 mL dose)

Bismuth subsalicylate 525 mg

Purpose

Upset stomach reliever and antidiarrheal

Uses

relieves

- travelers’ diarrhea
- diarrhea
- upset stomach due to overindulgence in food and drink, including:

heartburn
indigestion
nausea
gas
belching
fullness

WARNINGS

Reye’s syndrome: Children and teenagers who have or are recovering from chicken pox or flu-like symptoms should not use this product. When using this product, if changes in behavior with nausea and vomiting occur, consult a doctor because these symptoms could be an early sign of Reye’s syndrome, a rare but serious illness.

Allergy alert: Contains salicylate. Do not take if you are

- allergic to salicylates (including aspirin)
- taking other salicylate products

Do not use if you have

- an ulcer
- a bleeding problem
- bloody or black stool

Ask a doctor before use if you have

- fever
- mucus in the stool

Ask a doctor or pharmacist before use if you are taking any drug for

- anticoagulation (thinning the blood)
- diabetes
- gout
- arthritis

When using this product

a temporary, but harmless, darkening of the stool and/or tongue may occur

Stop use and ask a doctor if

- symptoms get worse or last more than 2 days
- ringing in the ears or loss of hearing occurs
- diarrhea lasts more than 2 days

If pregnant or breast-feeding,

ask a health professional before use.

Keep out of reach of children.

In case of overdose, get medical help or contact a Poison Control Center right away (1-800-222-1222).

Directions

- shake well before use
- only use dose cup provided
- adults and children 12 years and over:

30 mL (1 dose) every ½ hour or 60 mL (2 doses) every hour as needed for diarrhea / travelers’ diarrhea
30 mL (1 dose) every ½ hour as needed for overindulgence (upset stomach, heartburn, indigestion, nausea)

- do not exceed 8 doses (240 mL) in 24 hours
- use until diarrhea stops but not more than 2 days
- children under 12 years: ask a doctor
- drink plenty of clear fluids to help prevent dehydration caused by diarrhea

Other information

- each 30 mL dose contains: ■ sodium 5 mg ■ salicylate 199 mg
- keep tightly closed
- protect from freezing
- avoid excessive heat (over 104°F or 40°C)

Inactive ingredients

benzoic acid, flavor, glycerin, purified water, sucralose, xanthan gum

Questions or comments?

Call 1-888-287-1915